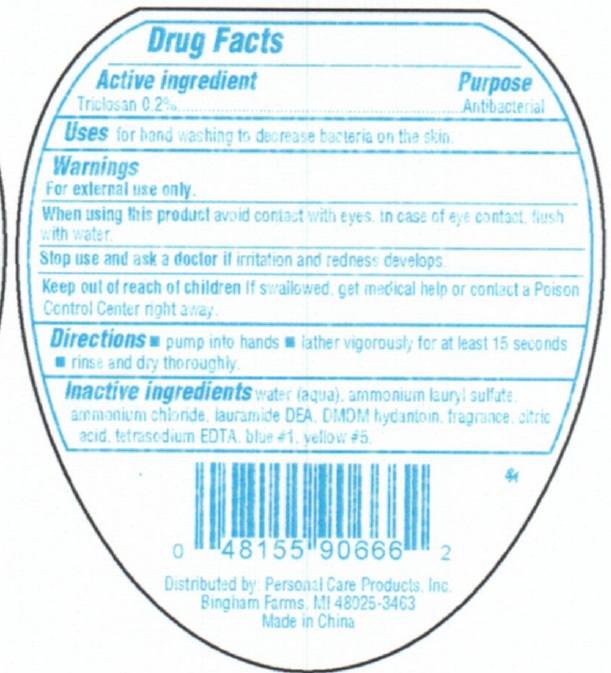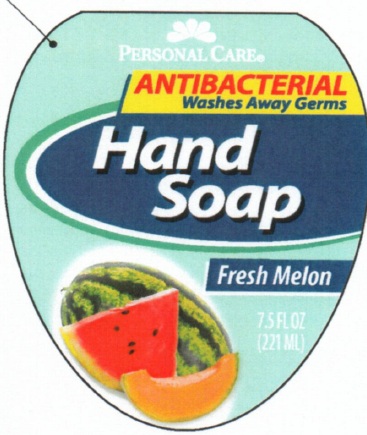 DRUG LABEL: Personal Care Antibacterial Hand - Fresh Melon
                        
NDC: 29500-9079 | Form: SOAP
Manufacturer: Personal Care Products, LLC
Category: otc | Type: HUMAN OTC DRUG LABEL
Date: 20111122

ACTIVE INGREDIENTS: TRICLOSAN 0.2 mL/100 mL
INACTIVE INGREDIENTS: WATER; AMMONIUM LAURYL SULFATE; AMMONIUM CHLORIDE; LAURIC DIETHANOLAMIDE; DMDM HYDANTOIN; CITRIC ACID MONOHYDRATE; EDETATE SODIUM; FD&C BLUE NO. 1; FD&C YELLOW NO. 5

Personal Care Antibacterial Hand Soap - Fresh Melon

Active Ingredient

Triclosan 0.2%

Purpose

Antibacterial

Uses

for handwashing to decrease bacteria on the skin

Warnings

For external use only

When using this product

Avoid contact with eyes. In case of eye contact, flush with water.

Stop use and ask a doctor

if irritation and redness develops

Keep out of reach of children

If swallowed get medical help or contact a Poison Control Center right away.

Directions

pump into hands

lather vigorously for at least 15 seconds

rinse and dry thoroughly

Inactive Ingredients

water (aqua), ammonium lauryl sulfate, ammonium chloride, lauramide DEA, DMDM hydantoin, fragrance, citric acid, tetrasodium EDTA, blue#1, yellow #5

PACKAGE LABEL

Personal Care

Antibacterial
Washes Away Germs

Hand soap
Fresh Melon 7.5 fl oz
(221ml)
Distributed by Personal Care Products, Inc.
Bingham Farms, MI 48205-3463
Made In China